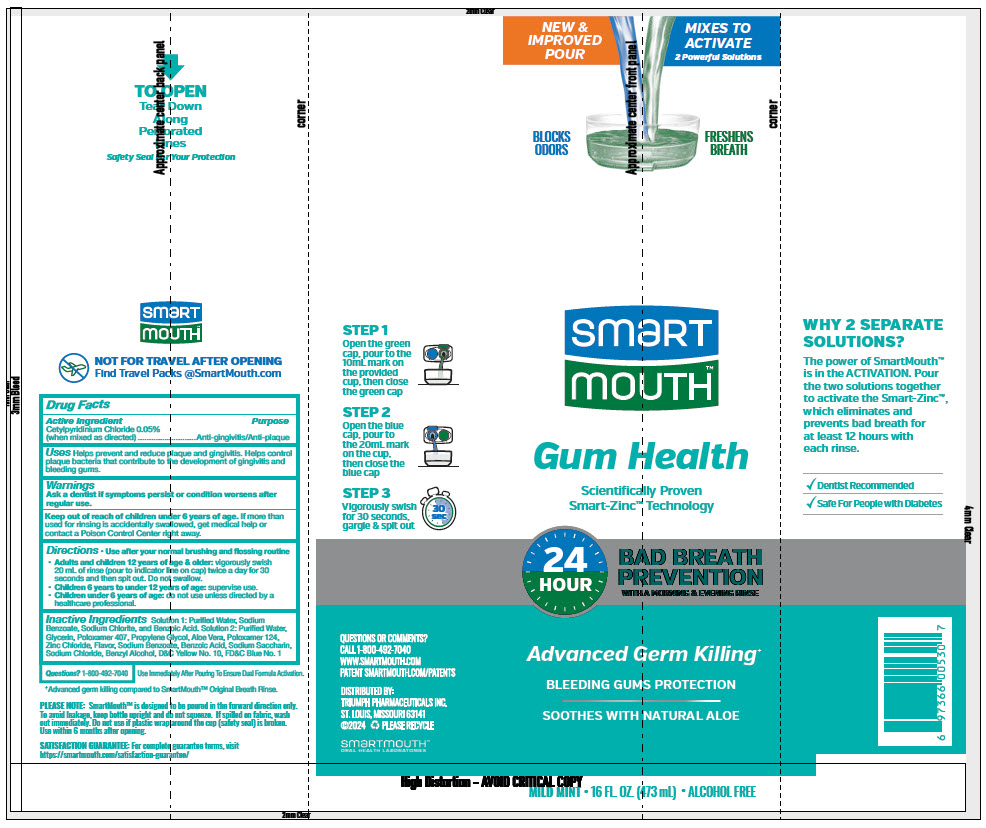 DRUG LABEL: SmartMouth  
NDC: 76357-509 | Form: KIT | Route: DENTAL
Manufacturer: Triumph Pharmaceuticals, Inc.
Category: otc | Type: HUMAN OTC DRUG LABEL
Date: 20241212

ACTIVE INGREDIENTS: Cetylpyridinium Chloride 500 mg/20 mL
INACTIVE INGREDIENTS: Water; Glycerin; Poloxamer 407; Propylene Glycol; ALOE; POLOXAMER 124; Zinc Chloride; SODIUM; Benzoic Acid; SACCHARIN SODIUM; Sodium Chloride; Benzyl Alcohol

SmartMouth™ Mouthwash
SmartMouth™ Gum Health Zinc Activated Formula

Drug Facts

Active Ingredient

Cetylpyridinium Chloride 0.05% (when mixed as directed)

Purpose

Anti-gingivitis/Anti-plaque

Uses

Helps prevent and reduce plaque and gingivitis. Helps control plaque bacteria that contribute to the development of gingivitis and bleeding gums.

Warnings

ASK DOCTOR

Ask a dentist if symptoms persist or condition worsens after regular use.

Keep out of reach of children under 6 years of age. If more than used for rinsing is accidentally swallowed, get medical help or contact a Poison Control Center right away.

Directions

- Use after your normal brushing and flossing routine
- Adults and children 12 years of age & older: vigorously swish 20 mL of rinse (pour to indicator line on cap) twice a day for 30 seconds and then spit out. Do not swallow.
- Children 6 years to under 12 years of age: supervise use.
- Children under 6 years of age: do not use unless directed by a healthcare professional.

Inactive Ingredients

Solution 1: Purified Water, Sodium Benzoate, Sodium Chlorite, and Benzoic Acid. Solution 2: Purified Water, Glycerin, Poloxamer 407, Propylene Glycol, Aloe Vera, Poloxamer 124, Zinc Chloride, Flavor, Sodium Benzoate, Benzoic Acid, Sodium Saccharin, Sodium Chloride, Benzyl Alcohol, D&C Yellow No. 10, FD&C Blue No. 1

Questions?

1-800-492-7040

DISTRIBUTED BY:
TRIUMPH PHARMACEUTICALS INC.
ST. LOUIS, MISSOURI 63141

PRINCIPAL DISPLAY PANEL - Kit Label

NEW &
IMPROVED
POUR

MIXES TO
ACTIVATE
2 Powerful Solutions

BLOCKS
ODORS
FRESHENS
BREATH

smart
mouth™

Gum Health
Scientifically Proven
Smart-Zinc™ Technology

24
HOUR

BAD BREATH
PREVENTION
WITH A MORNING & EVENING RINSE

Advanced Germ Killing^+
BLEEDING GUMS PROTECTION
SOOTHES WITH NATURAL ALOE

MILD MINT • 16 FL. OZ. (473 mL) • ALCOHOL FREE